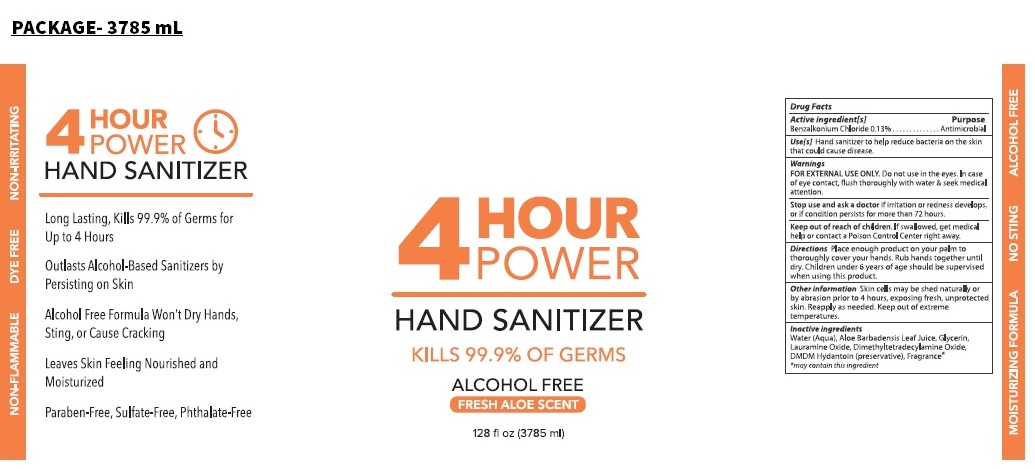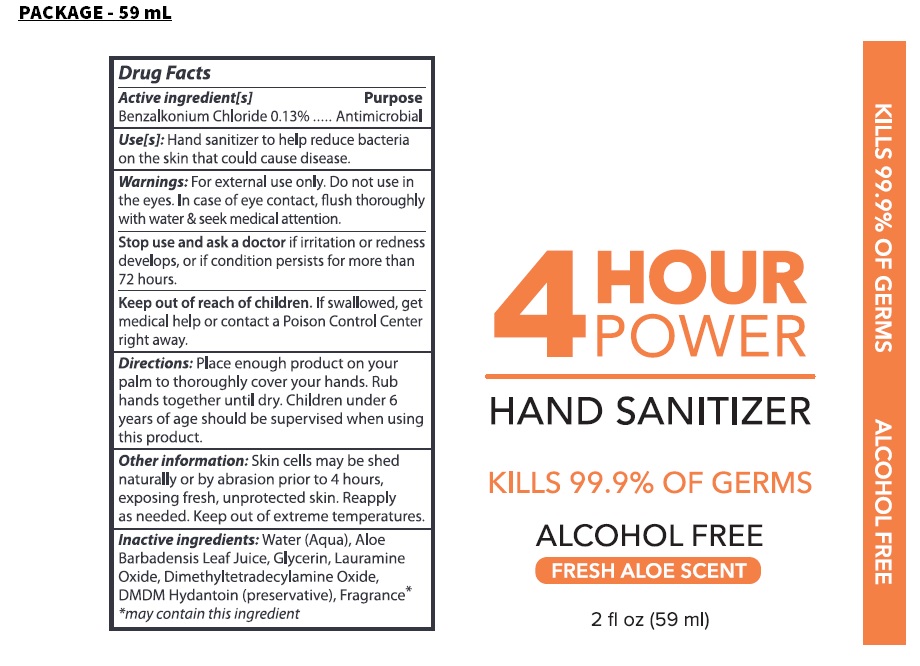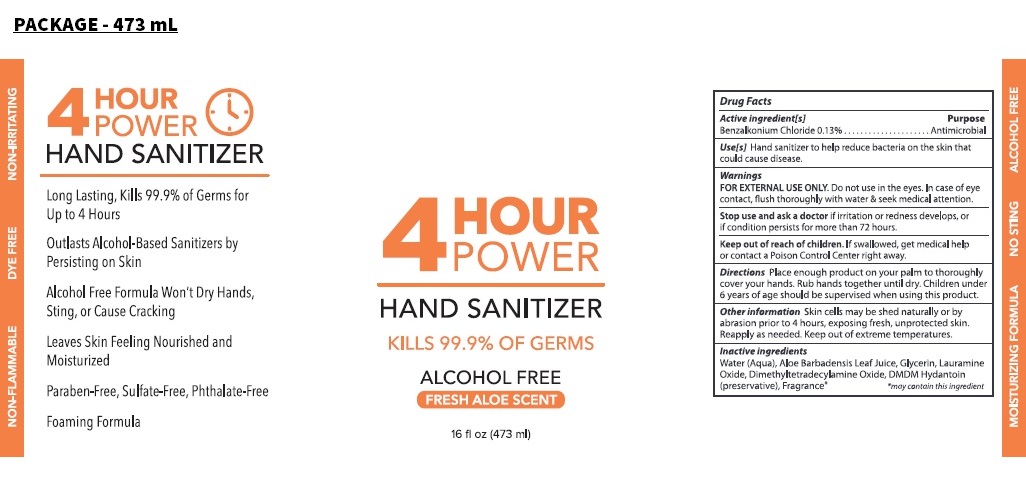 DRUG LABEL: 4 Hour Power Hand Sanitizer
NDC: 77042-440 | Form: LIQUID
Manufacturer: Guide Energy Solutions LLC
Category: otc | Type: HUMAN OTC DRUG LABEL
Date: 20210406

ACTIVE INGREDIENTS: BENZALKONIUM CHLORIDE 0.13 g/100 mL
INACTIVE INGREDIENTS: WATER; ALOE VERA LEAF; GLYCERIN; LAURAMINE OXIDE; MYRISTAMINE OXIDE; DMDM HYDANTOIN

4 Hour Power Hand Sanitizer

Active ingredient[s]

Benzalkonium Chloride 0.13%

Purpose

Antimicrobial

Use[s]

Hand sanitizer to help reduce bacteria on the skin that could cause disease.

Warnings

FOR EXTERNAL USE ONLY. Do not use in the eyes. In case of eye contact, flush thoroughly with water & seek medical attention.
Stop use and ask a doctor if irritation or redness develops, or if condition persists for more than 72 hours.

Keep out of reach of children. If swallowed, get medical help or contact a Poison Control Center right away.

Directions

Place enough product on your palm to thoroughly cover your hands. Rub hands together until dry. Children under 6 years of age should be supervised when using this product.

Other information

Skin cells may be shed naturally or by abrasion prior to 4 hours, exposing fresh, unprotected skin. Reapply as needed. Keep out of extreme temperatures.

Inactive ingredients

Water (Aqua), Aloe Barbadensis Leaf Juice, Glycerin, Lauramine Oxide, Dimethyltetradecylamine Oxide, DMDM Hydantoin (preservative), Fragrance*
*may contain this ingredient

KILLS 99.9% OF GERMS

ALCOHOL FREE

FRESH ALOE SCENT

NON-FLAMMABLE

DYE FREE

NON-IRRITATING

MOISTURIZING FORMULA

NO STING

Long Lasting, Kills 99.9% of Germs for Up to 4 Hours

Outlasts Alcohol-Based Sanitizers by Persisting on Skin

Alcohol Free Formula Won't Dry Hands, Sting, or Cause Cracking

Leaves Skin Feeling Nourished and Moisturized

Paraben-Free, Sulfate-Free, Phthalate-Free

Foaming Formula